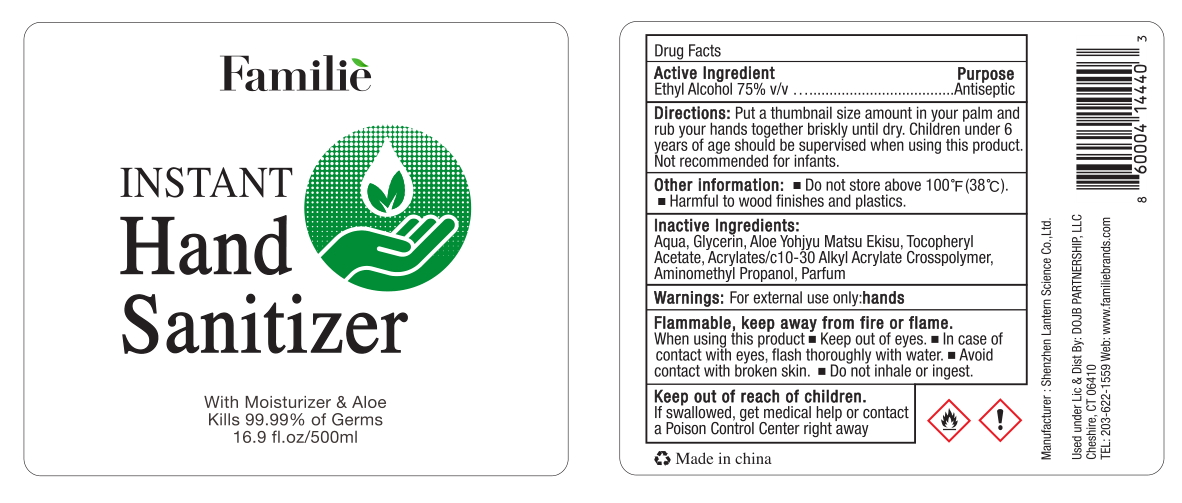 DRUG LABEL: Familie hand sanitizer 500ml
NDC: 54860-284 | Form: LIQUID
Manufacturer: Shenzhen Lantern Science Co.,Ltd
Category: otc | Type: HUMAN OTC DRUG LABEL
Date: 20200830

ACTIVE INGREDIENTS: ALCOHOL 75 mL/100 mL
INACTIVE INGREDIENTS: .ALPHA.-TOCOPHEROL ACETATE 0.01 mL/100 mL; ALOE 0.15 mL/100 mL; WATER 23.85 mL/100 mL; ALOE ANDONGENSIS WHOLE 0.1 mL/100 mL; AMINOMETHYLPROPANOL 0.09 mL/100 mL; CARBOMER INTERPOLYMER TYPE A (55000 CPS) 0.3 mL/100 mL; GLYCERIN 0.5 mL/100 mL

Familie hand sanitizer 500ml

Active Ingredient

Ethyl Alochol 75% v/v

purpose

antiseptic

DOSAGE AND ADMINISTRATION

Recommended for repeated use.

use anywhere without water.

Warning

For external use only:hands

flammable,keep away from heat and flame.

WARNINGS AND PRECAUTIONS

For external use only.

Flammable, keep away from heat and flame.

STOP USE

Discontinue if skin becomes irritated and ask a doctor .

Keep out of reach of children. In case of accidental ingestion, seek professional assistance or contact a poson control center immediately.

Inactive ingredients

water,Glycerin,Aloe Yohjyu Mastu Ekisu,Tocopheryl Acetate,Acrylates/C10-30 Alkyl Acrylate Crosspolymer,Aminomethyl Propanol,Parfum.

directions

Put a thumbnail size amount in your palm and rub your hands together briskly until dry.Children under 6 years of age should be supervised when using this product.Not recommended for infants.

When using this product

keep out of eyes. In case of contact with eyes, flush thoroughly with water.

Do not inhale or ingest.

Avoid contact with broken skin.

Other information

Do not store above 105F.

May discolor some fabrics.

Harmful to wood finishes and plastics.

other information

Do not store above100℉（38℃）

Harmful to wood finishes and plastics.

When using this product

Keep out of eyes,In case of contact with eyes,flush thoroughly with water.

Avoid contact with broken skin.

Do not inhale or ingest.

Keep out of reach of children

If swallowed,get medical help or contact a Poison Control Center right away.